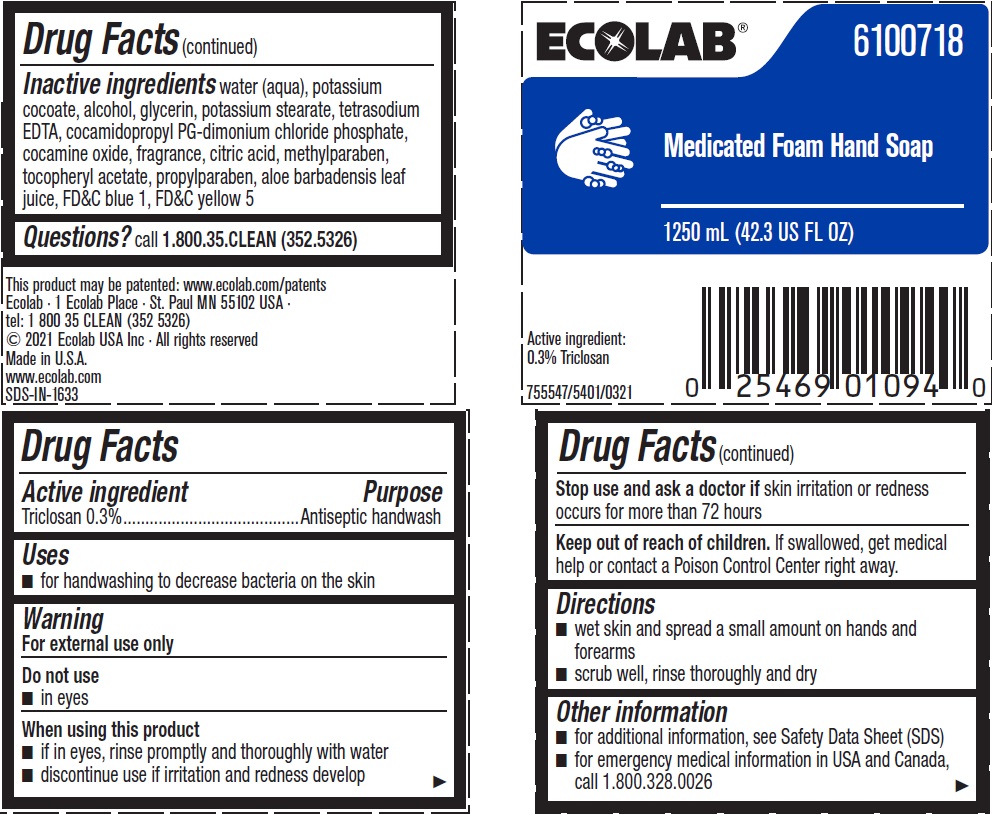 DRUG LABEL: Ecolab
NDC: 47593-469 | Form: SOLUTION
Manufacturer: Ecolab Inc.
Category: otc | Type: HUMAN OTC DRUG LABEL
Date: 20240416

ACTIVE INGREDIENTS: TRICLOSAN 3 mg/1 mL
INACTIVE INGREDIENTS: WATER; POTASSIUM COCOATE; ALCOHOL; GLYCERIN; POTASSIUM STEARATE; EDETATE SODIUM; COCAMIDOPROPYL PG-DIMONIUM CHLORIDE PHOSPHATE; COCAMINE OXIDE; CITRIC ACID MONOHYDRATE; METHYLPARABEN; .ALPHA.-TOCOPHEROL ACETATE, D- ; PROPYLPARABEN; ALOE VERA LEAF; FD&C BLUE NO. 1; FD&C YELLOW NO. 5

Drug Facts

Active ingredient

Triclosan 0.3%

Purpose

Antiseptic handwash

Uses

- for handwashing to decrease bacteria on the skin

Warnings

For external use only

Do not use

- in eyes

When using this product

- if in eyes, rinse promptly and thoroughly with water
- discontinue use if irritation and redness develop

Stop use and ask a doctor if

- skin irritation or redness occurs for more than 72 hours

Keep out of reach of children. If swallowed, get medical help or contact a Poison Control Center right away.

Directions

- wet skin and spread a small amount on hands and forearms
- scrub well, rinse thoroughly and dry

Other information

- for additional information, see Safety Data Sheet (SDS)
- for emergency medical information in USA and Canada, call 1.800.328.0026

INACTIVE INGREDIENT

Inactive ingredients water (aqua), potassium cocoate, alcohol, glycerin, potassium stearate, tetrasodium EDTA, cocamidopropyl PG-dimonium chloride phosphate, cocamine oxide, fragrance, citric acid, methylparaben, tocopheryl acetate, propylparaben, aloe barbadensis leaf juice, FD&C blue 1, FD&C yellow 5

Questions? call 1.800.35.CLEAN (352.5326)

Principal display panel and representative label

ECOLAB®

6100718

Medicated Foam Hand Soap

1250 ml (42.3 US FL OZ)

Active Ingredient: 0.3% Triclosan

1 Ecolab Place · St. Paul MN 55102 USA

tel: 1 800 35 CLEAN (352 5326)

© 2021 Ecolab USA Inc · All rights reserved

Made in U.S.A.

www.ecolab.com

SDS-IN-1633